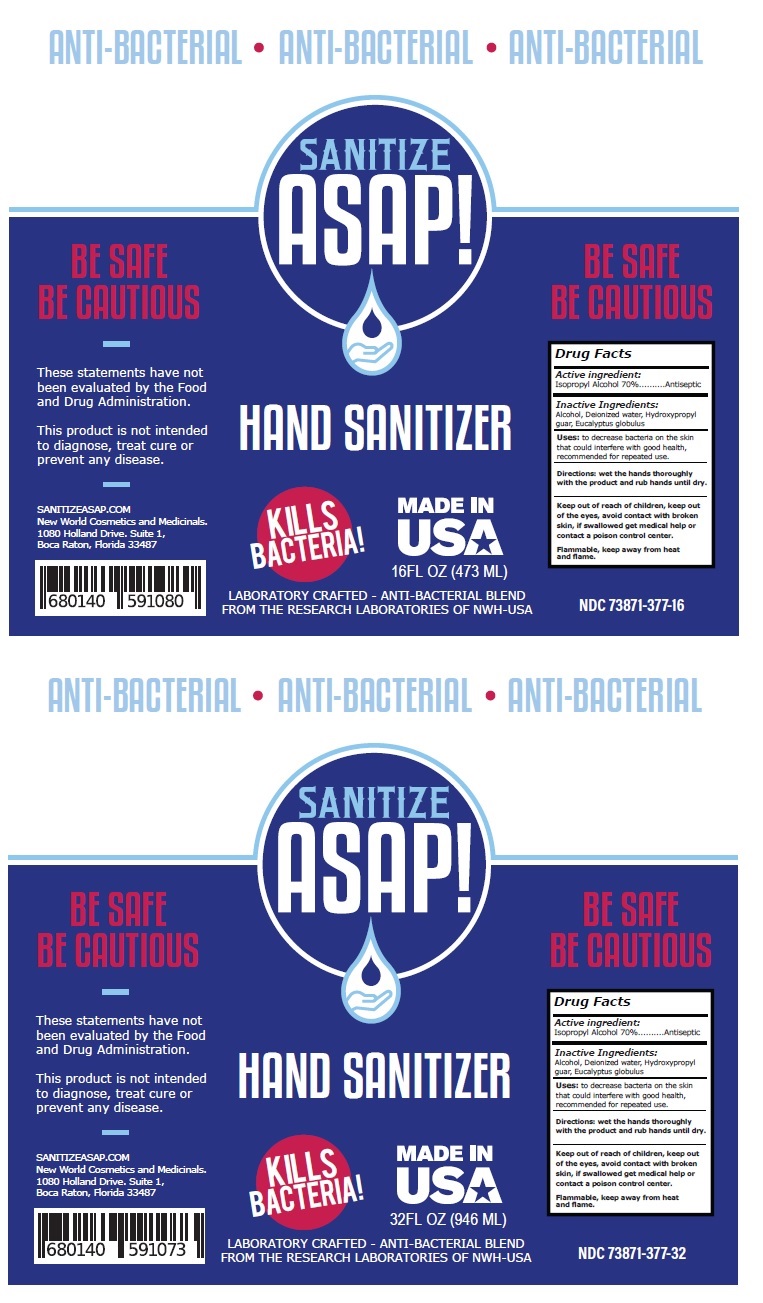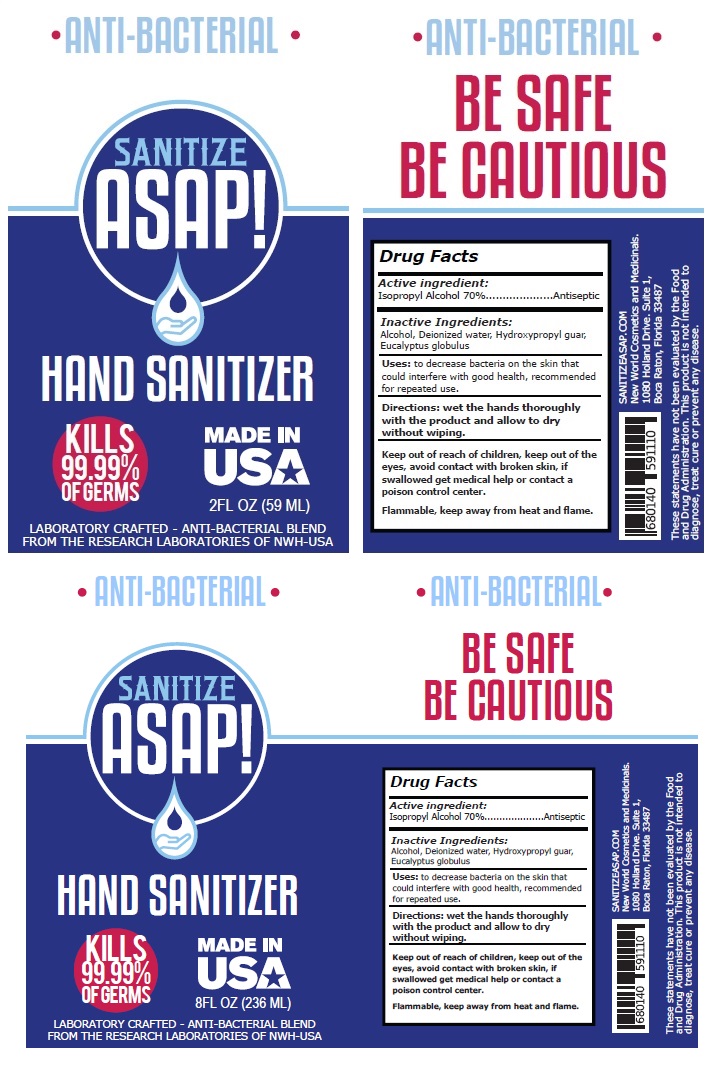 DRUG LABEL: SANITIZE ASAP HAND SANITIZER
NDC: 73871-377 | Form: GEL
Manufacturer: New World Holdings, Inc.
Category: otc | Type: HUMAN OTC DRUG LABEL
Date: 20200406

ACTIVE INGREDIENTS: ISOPROPYL ALCOHOL 70 mL/100 mL
INACTIVE INGREDIENTS: ALCOHOL; WATER; GUARAPROLOSE (3500 MPA.S AT 1%); EUCALYPTUS GLOBULUS LEAF

SANITIZE ASAP HAND SANITIZER

Active ingredient:

Isopropyl Alcohol 70%

Purpose

Antiseptic

INDICATIONS AND USAGE

Uses: to decrease bacteria on the skin that could interfere with good health, recommended for repeated use.

Warnings

Flammable, keep away from heat and flame.

Keep out of reach of children, keep out of the eyes, avoid contact with broken skin, if swallowed get medical help or contact a poison control center.

DOSAGE AND ADMINISTRATION

Directions: wet the hands thoroughly with the product and allow to dry without wiping.

Inactive Ingredients:

Alcohol, Deionized water, Hydroxypropyl guar, Eucalyptus globulus

ANTI-BACTERIAL

KILLS 99.99% OF GERMS

MADE IN USA

LABORATORY CRAFTED - ANTI-BACTERIAL BLEND FROM THE RESEARCH LABORATORIES OF NWH.

BE SAFE BE CAUTIOUS

SANITIZEASAP.COM

New World Cosmetics and Medicinals.

1080 Holland Drive. Suite 1

Boca Raton, Florida 33487

These statements have not been evaluated by the Food and Drug Administration. This product is not intended to diagnose, treat cure or prevent any disease.